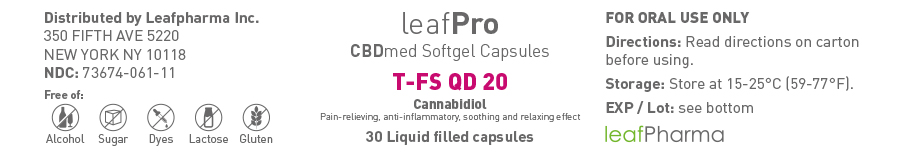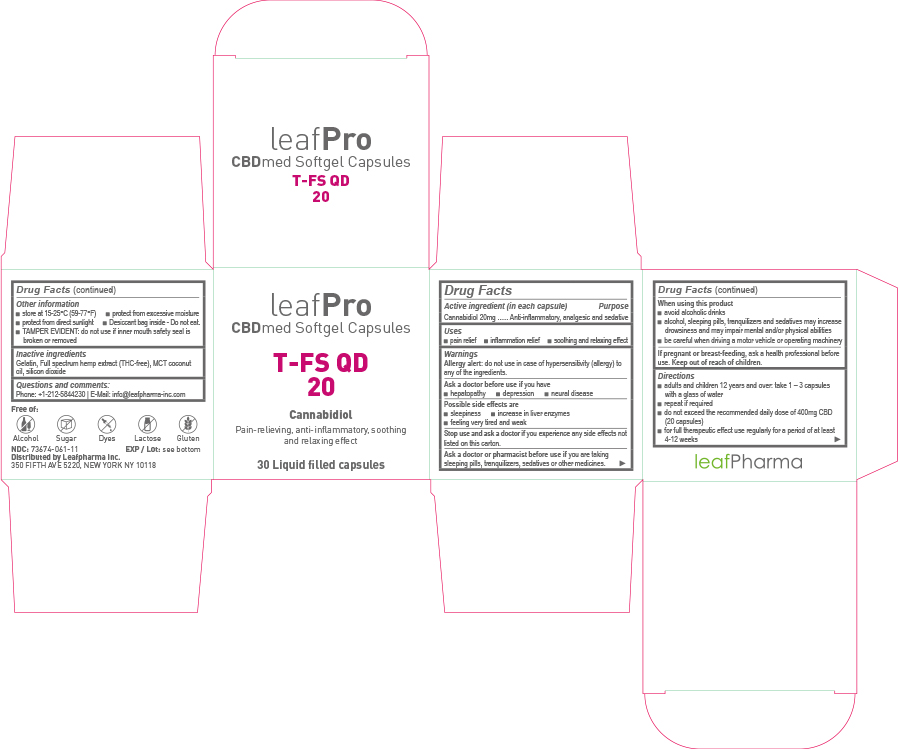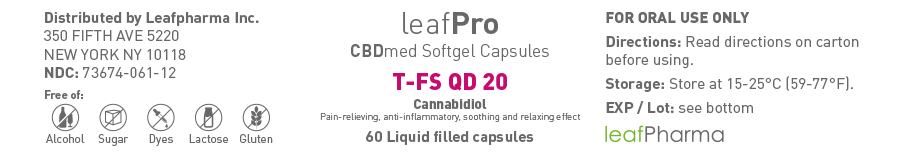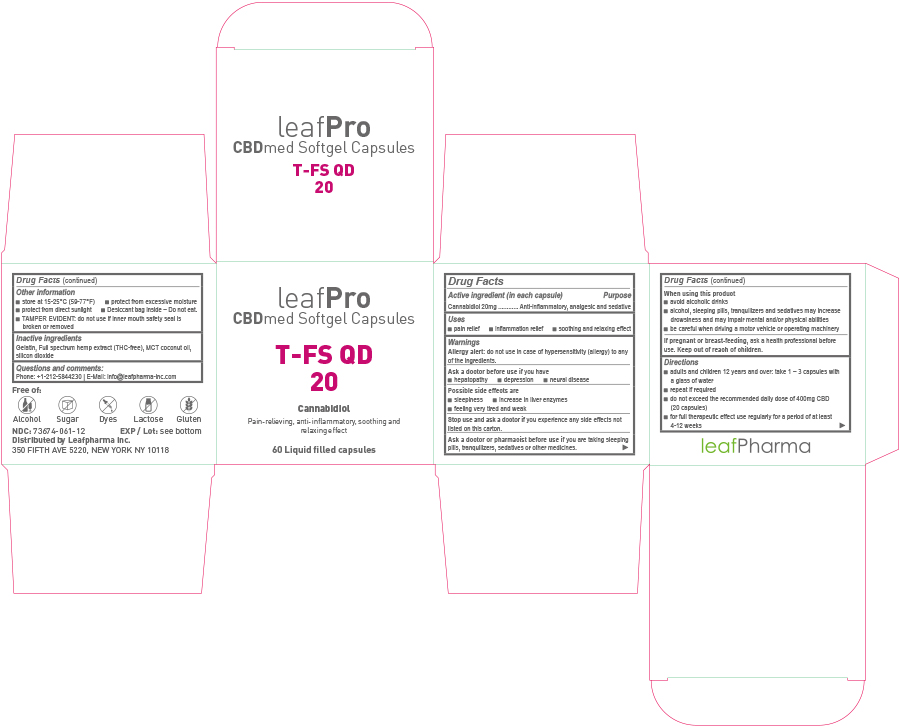 DRUG LABEL: leafPro CBDmed Softgels T-FS QD 20
NDC: 73674-061 | Form: CAPSULE, LIQUID FILLED
Manufacturer: leafMed GmbH
Category: otc | Type: HUMAN OTC DRUG LABEL
Date: 20200319
DEA Schedule: CV

ACTIVE INGREDIENTS: CANNABIDIOL 20 mg/1 1
INACTIVE INGREDIENTS: HEMP; SILICON DIOXIDE; MEDIUM-CHAIN TRIGLYCERIDES; GELATIN, UNSPECIFIED

leafPro CBDmed Softgel Capsules T-FS QD 20

Drug Facts

Active Ingredient (in each capsule)

Cannabidiol 20mg

Purpose

Anti-inflammatory, analgesic and sedative

Uses

- pain relief
- inflammation relief
- soothing and relaxing effect

Warnings

Allergy alert:

do not use in case of hypersensitivity (allergy) to any of the ingredients.

Ask a doctor before use if

you have

- hepatopathy
- depression
- neural disease

Possible side effects are

- sleepiness
- increase in liver enzymes
- feeling very tired and weak

Stop use and ask a doctor if

you experience any side effects not listed on this carton.

Ask a doctor or pharmacist before use if

you are taking sleeping pills, tranquilizers, sedatives or other medicines.

When using this product

- avoid alcoholic drinks
- alcohol, sleeping pills, tranquilizers and sedatives may increase drowsiness and may impair mental and/or physical abilities
- be careful when driving a motor vehicle or operating machinery

If pregnant or breast-feeding,

ask a health professional before use.

Directions

- adults and children 12 years and over: take 1 – 3 capsules with a glass of water
- repeat procedure if required
- do not exceed the recommended daily dose of 400mg CBD (20 capsules)
- for full therapeutic effect use regularly for a period of at least 4-12 weeks

Other information

- store at 15-25°C (59-77°F)
- protect from excessive moisture
- protect from direct sunlight
- Desiccant bag inside – Do not eat.
- TAMPER EVIDENT: do not use if inner mouth safety seal is broken or removed

Inactive ingredients:

Gelatin, full spectrum hemp extract (THC-free), MCT coconut oil, silicon dioxide

Questions and comments:

Phone: +1-212-5844230

E-Mail: info@leafpharma-inc.com

Principal Display Panel - 30 Liquid filled capsules

leaf Pro
CBDmed Softgel Capsules
T-FS QD
20
Cannabidiol
Pain-relieving, anti-inflammatory, soothing and relaxing effect
30 Liquid filled capsules

Principal display panal - 60 Liquid filled capsules

leaf Pro
CBDmed Softgel Capsules
T-FS QD
20

Cannabidiol
Pain-relieving, anti-inflammatory, soothing and relaxing effect
60 Liquid filled capsules